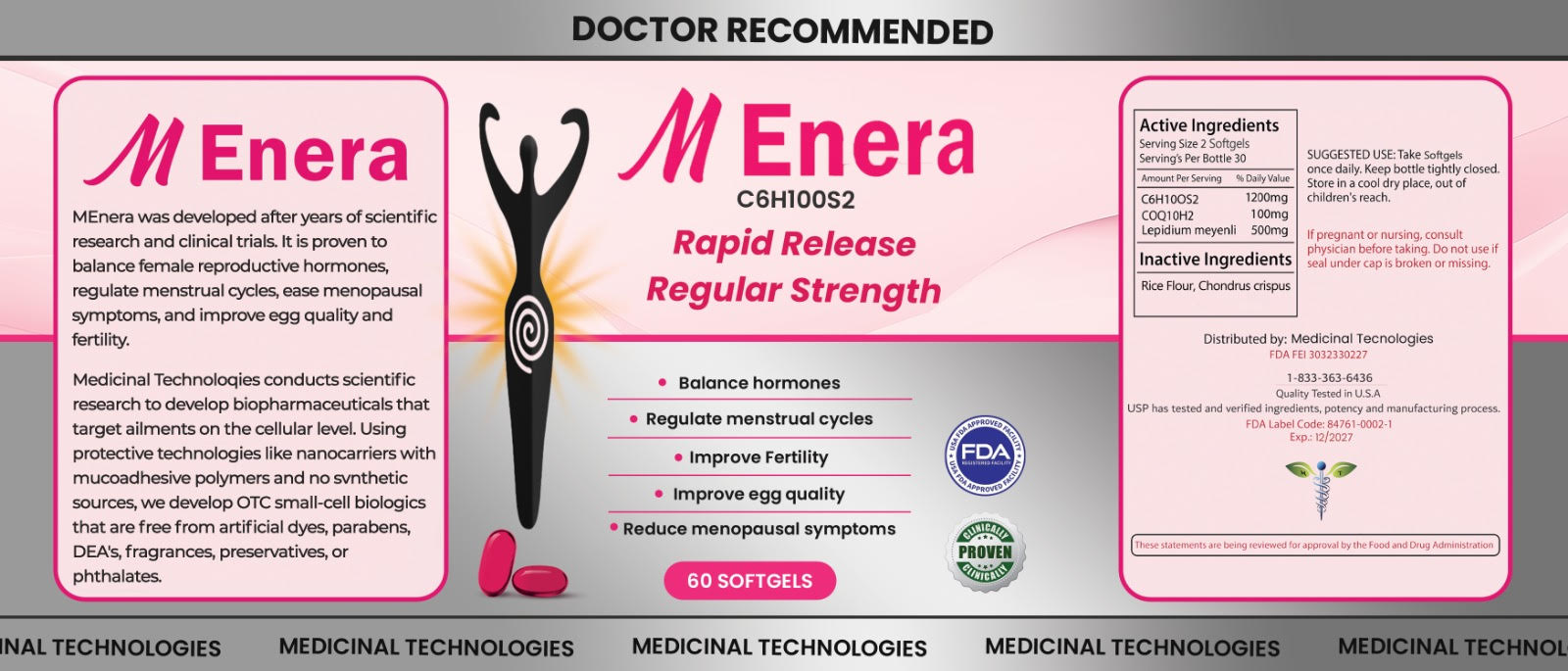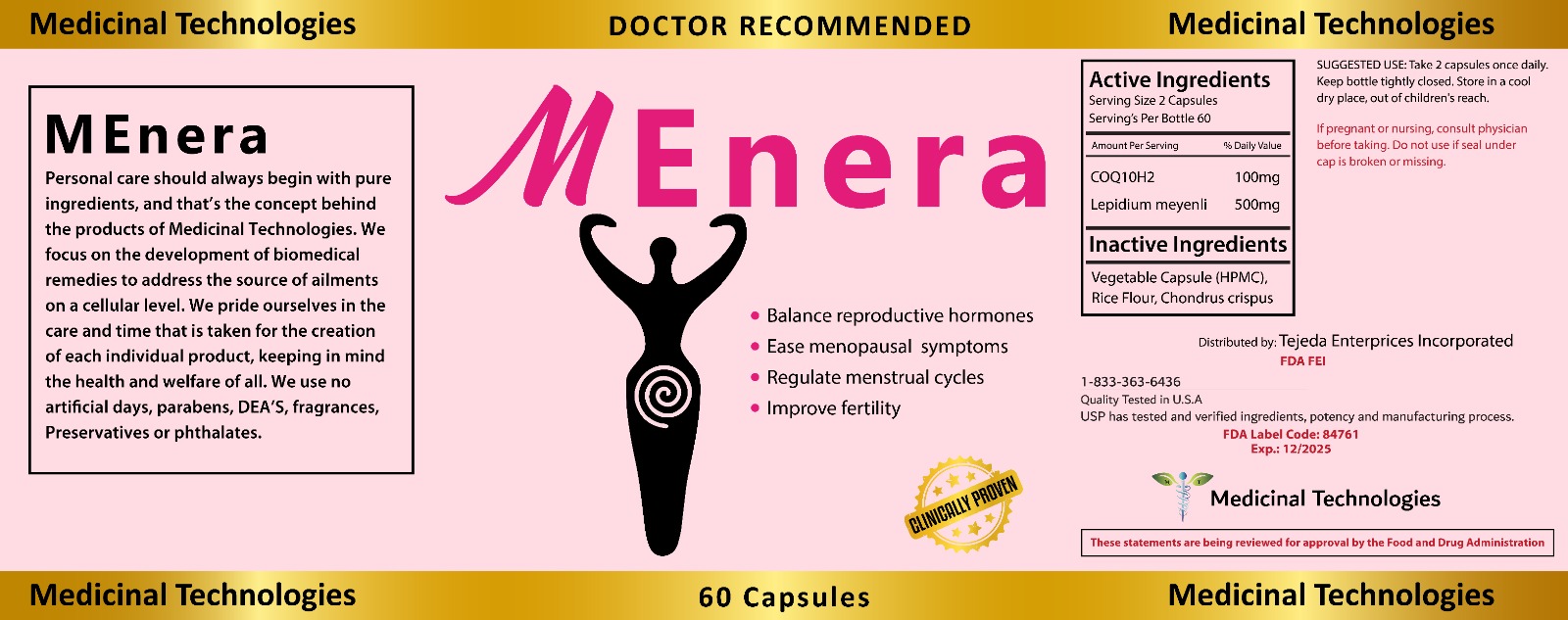 DRUG LABEL: MEnera
NDC: 84761-0004 | Form: CAPSULE
Manufacturer: Tejeda Enterprises Incorporated
Category: otc | Type: HUMAN OTC DRUG LABEL
Date: 20251229

ACTIVE INGREDIENTS: ALLICIN 1200 mg/2 U; UBIQUINOL 100 mg/2 U; LEPIDIUM MEYENII ROOT 500 mg/2 U
INACTIVE INGREDIENTS: HYDROGENATED SOYBEAN LECITHIN; POLYETHYLENE GLYCOL, UNSPECIFIED

DOSAGE AND ADMINISTRATION

SUGGESTED USE: Take 2 capsules once daily.

WARNINGS

Keep bottle tightly closed. Store in a cool dry place, out of children's reach.
If pregnant or nursing, consult physician before taking. Do not use if seal under cap is broken or missing.

INACTIVE INGREDIENT

Rice Flour, Chondrus crispus

INDICATIONS AND USAGE

Medicinal Technologies
MEnera
Personal care should always begin with pure ingredients, and that's the concept behind the products of Medicinal Technologies. We focus on the development of biomedical remedies to address the source of ailments on a cellular level. We pride ourselves in the care and time that is taken for the creation of each individual product, keeping in mind the health and welfare of all. We use no artificial days, parabens, DEA'S, fragrances, Preservatives or phthalates.
DOCTOR RECOMMENDED
MEnera
Balance reproductive hormones
Ease menopausal symptoms
Regulate menstrual cycles • Improve fertility
Medicinal Technologies
CLINICALLY PROVEN
60 Capsules

Keep out of children's reach.

PURPOSE

Balance reproductive hormones
Ease menopausal symptoms
Regulate menstrual cycles

Improve fertility

ACTIVE INGREDIENT

UBIQUINOL
Lepidium meyenli

PACKAGE LABEL

Content of Labling